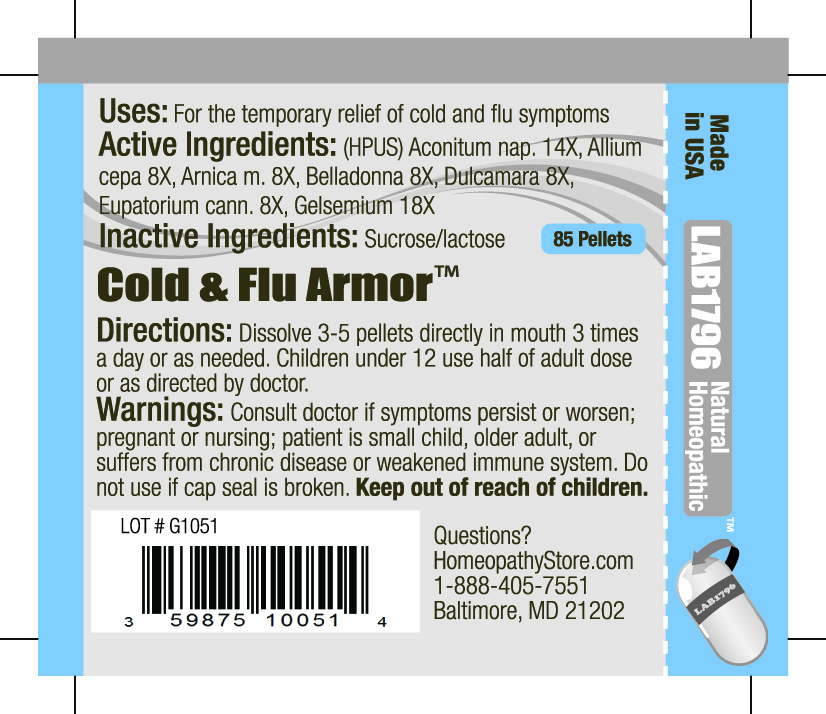 DRUG LABEL: Lab1796 Cold and Flu Armor
NDC: 59875-1005 | Form: PELLET
Manufacturer: HomeopathyStore.com
Category: homeopathic | Type: HUMAN OTC DRUG LABEL
Date: 20101217

ACTIVE INGREDIENTS: ACONITUM NAPELLUS 14 [hp_X]/1 1; ONION 8 [hp_X]/1 1; ARNICA MONTANA 8 [hp_X]/1 1; ATROPA BELLADONNA 8 [hp_X]/1 1; SOLANUM DULCAMARA TOP 8 [hp_X]/1 1; EUPATORIUM CANNABINUM WHOLE FLOWERING 8 [hp_X]/1 1; GELSEMIUM SEMPERVIRENS ROOT 18 [hp_X]/1 1
INACTIVE INGREDIENTS: SUCROSE; LACTOSE

Cold and Flu Armor

Uses:

For the temporary relief of cold and flu symptoms

Active Ingredients:

(HPUS) Aconitum nap. 14X, Allium cepa 8X, Arnica m. 8X, Belladonna 8X, Dulcamara 8X, Eupatorium cann. 8X, Gelsemium 18X

Inactive Ingredients:

Sucrose/lactose

Directions:

Enter section text here

DOSAGE AND ADMINISTRATION

Dissolve 3-5 pellets directly in mouth 3 times a day or as needed. Children under 12 use half of adult dose or as directed by doctor.

Warnings:

Consult doctor if symptoms persist or worsen; pregnant or nursing; patient is small child, older adult, or suffers from chronic disease or weakened immune system. Do not use if cap seal is broken.

Keep out of reach of children.

PACKAGE LABEL

Enter section text here